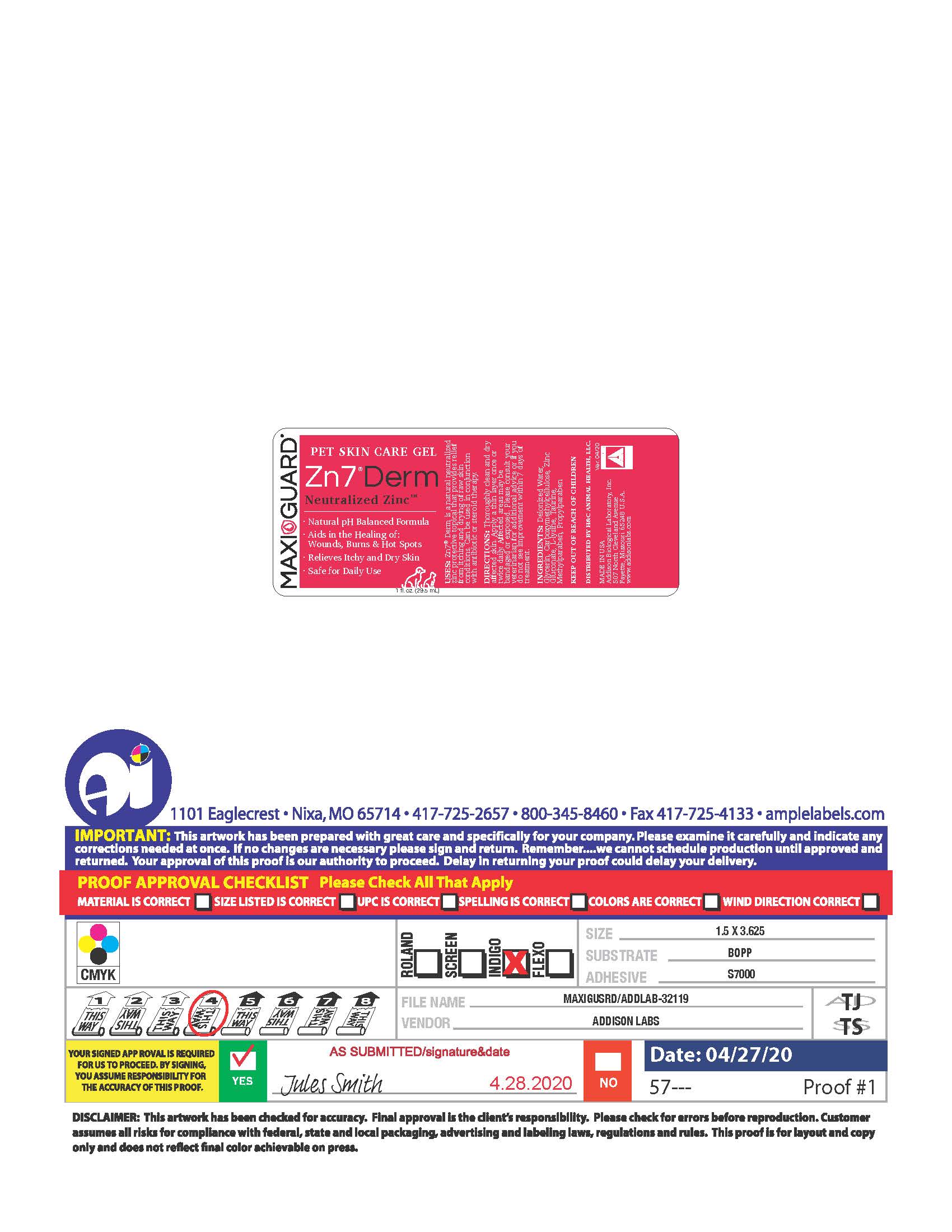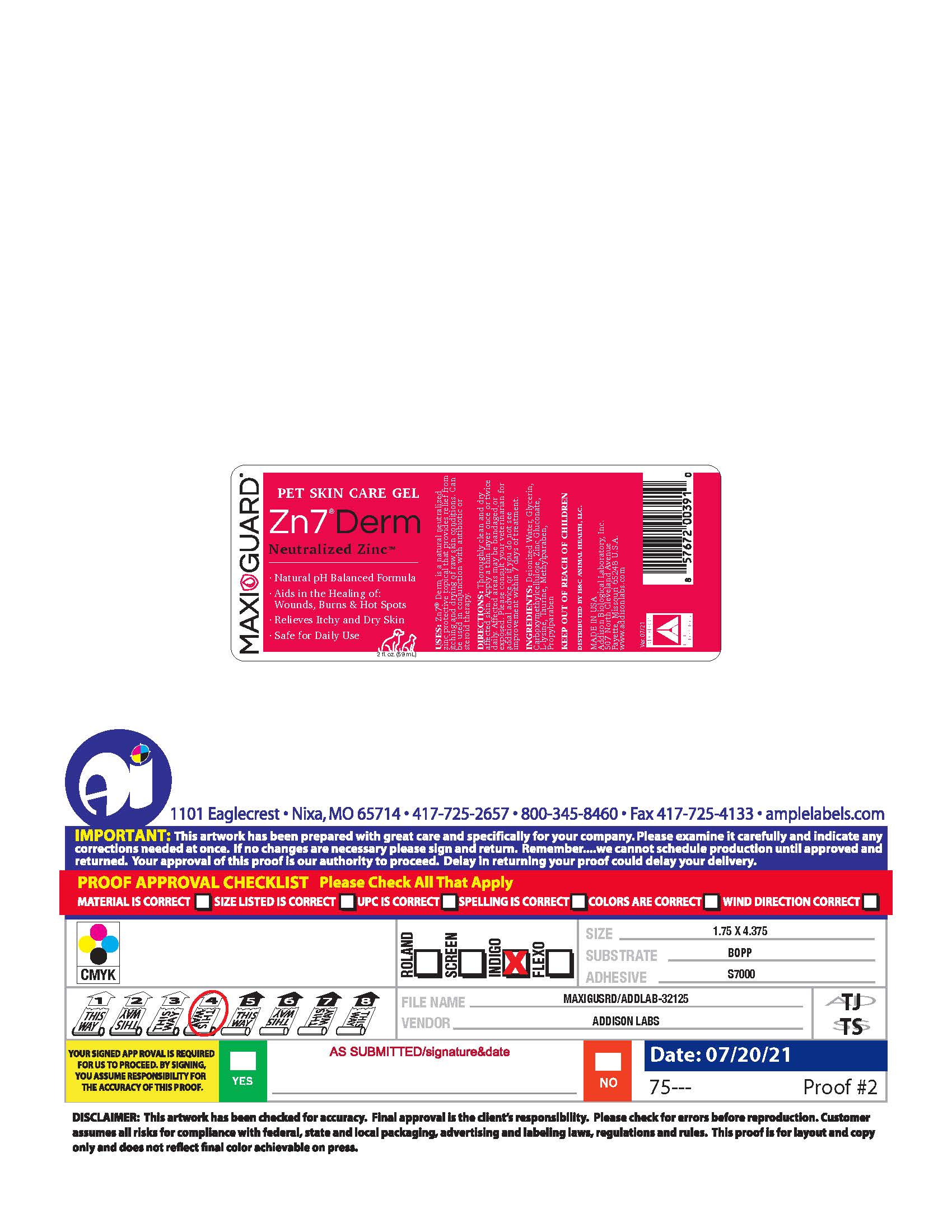 DRUG LABEL: Zn7 Derm
NDC: 86137-7409 | Form: GEL
Manufacturer: H&C Animal Health
Category: animal | Type: OTC ANIMAL DRUG LABEL
Date: 20251201

ACTIVE INGREDIENTS: ZINC GLUCONATE .011 g/1 mL
INACTIVE INGREDIENTS: WATER; TAURINE; METHYLPARABEN; PROPYLPARABEN; LYSINE; GLYCERIN; CARBOXYMETHYLCELLULOSE

Zn7®Derm

INDICATIONS AND USAGE

USES: Zn7® Derm is natural neutralized zinc topical that provides relief from itching and drying of raw skin conditions. Can be used in conjunction with antibiotic or steroid therapy.

INSTRUCTIONS FOR USE

DIRECTIONS: Thoroughly clean and dry affected skin. Apply a thin layer once or twice daily. Affected areas may be bandaged or exposed. Please consult your veterinarian for additional advice or if you do not see improvement within 7 days of treatment.

INGREDIENTS: Deionized Water, Glycerin, Carboxymethycellulose, Zinc Gluconate, L-Lysine, Taurine, Methylparaben, Propylparaben.

Keep out of reach of children.

DISTRIBUTED BY H&C ANIMAL HEALTH, LLC.

MADE IN USA

Addison Biological Laboratory, Inc.
507 North Cleveland Avenue
Fayette, Missouri 65248 U.S.A.
www.addisonlabs.com

PACKAGE LABEL

PET SKIN CARE GEL
Zn7®Derm
Neutralized Zinc
Natural pH Balanced Formula
Aids in the Healing of: Wounds, Burns & Hot Spots
Relieves Itchy and Dry Skin
Safe for Daily Use
1 fl.oz. (29.5mL)
USES: Zn7Derm is natural neutralized zinc topical that provides relief from itching and drying of raw skin conditions. Can be used in conjunction with antibiotic or steroid treatment.
DIRECTIONS: Thoroughly clean and dry affected skin. Apply a thin layer once or twice daily. Affected areas may be bandaged or exposed. Please consult your veterinarian for additional advice or if you do not see improvement within 7 days of treatment.
INGREDIENTS: Deionized Water, Glycerin, Carboxymethycellulose, Zinc Gluconate, L-Lysine, Taurine, Methylparaben, Propyl
Keep out of reach of children
DISTRIBUTED BY H&C ANIMAL HEALTH, LLC.
MADE IN USA
Addison Biological Laboratory, Inc.
507 North Cleveland Avenue
Fayette, Missouri 65248
www.addisonlabs.com
Rev. 04/20

PACKAGE LABEL

PET SKIN CARE GEL
Zn7®Derm
Neutralized ZincTM
Natural pH Balanced Formula
Aids in the Healing of: Wounds, Burns & Hot Spots
Relieves Itchy and Dry Skin
Safe for Daily Use
2 fl.oz. (59mL)
USES: Zn7®Derm is natural neutralized zinc protective topical that provides relief from itching and drying of raw skin conditions. Can be used in conjunction with antibiotic or steroid therapy.
DIRECTIONS: Thoroughly clean and dry affected skin. Apply a thin layer once or twice daily. Affected areas may be bandaged or exposed. Please consult your veterinarian for additional advice or if you do not see improvement within 7 days of treatment.
INGREDIENTS: Deionized Water, Glycerin, Carboxymethycellulose, Zinc Gluconate, L-Lysine, Taurine, Methylparaben, Propyl
Keep out of reach of children
DISTRIBUTED BY H&C ANIMAL HEALTH, LLC.
MADE IN USA
Addison Biological Laboratory, Inc.
507 North Cleveland Avenue
Fayette, Missouri 65248
www.addisonlabs.com
Rev. 07/21